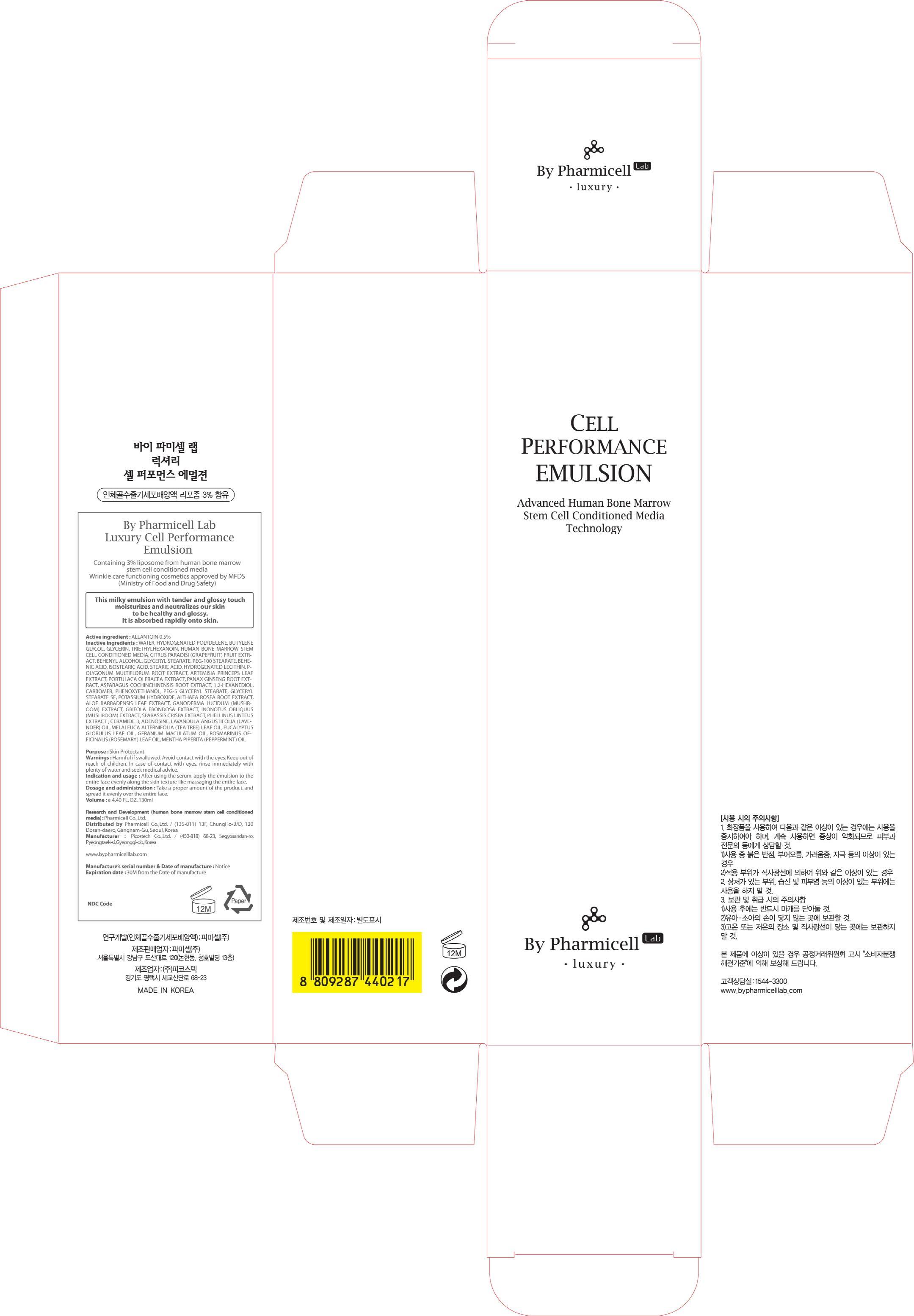 DRUG LABEL: Luxury Cell Performance Emulsion
NDC: 60949-130 | Form: CREAM
Manufacturer: Pharmicell Co., Ltd.
Category: otc | Type: HUMAN OTC DRUG LABEL
Date: 20140922

ACTIVE INGREDIENTS: ALLANTOIN 0.65 mg/130 mL
INACTIVE INGREDIENTS: WATER; BUTYLENE GLYCOL

ACTIVE INGREDIENT

Active ingredient : ALLANTOIN 0.5%

INACTIVE INGREDIENT

Inactive ingredients : WATER, HYDROGENATED POLYDECENE, BUTYLENE GLYCOL, GLYCERIN, TRIETHYLHEXANOIN, HUMAN BONE MARROW STEM CELL CONDITIONED MEDIA, CITRUS PARADISI (GRAPEFRUIT) FRUIT EXTRACT, BEHENYL ALCOHOL, GLYCERYL STEARATE, PEG-100 STEARATE, BEHENIC ACID, ISOSTEARIC ACID, STEARIC ACID, HYDROGENATED LECITHIN, POLYGONUM MULTIFLORUM ROOT EXTRACT, ARTEMISIA PRINCEPS LEAF EXTRACT, PORTULACA OLERACEA EXTRACT, PANAX GINSENG ROOT EXTRACT, ASPARAGUS COCHINCHINENSIS ROOT EXTRACT, 1,2-HEXANEDIOL, CARBOMER, PHENOXYETHANOL, PEG-5 GLYCERYL STEARATE, GLYCERYL STEARATE SE, POTASSIUM HYDROXIDE, ALTHAEA ROSEA ROOT EXTRACT, ALOE BARBADENSIS LEAF EXTRACT, GANODERMA LUCIDUM (MUSHROOM) EXTRACT, GRIFOLA FRONDOSA EXTRACT, INONOTUS OBLIQUUS (MUSHROOM) EXTRACT, SPARASSIS CRISPA EXTRACT, PHELLINUS LINTEUS EXTRACT , CERAMIDE 3, ADENOSINE, LAVANDULA ANGUSTIFOLIA (LAVENDER) OIL, MELALEUCA ALTERNIFOLIA (TEA TREE) LEAF OIL, EUCALYPTUS GLOBULUS LEAF OIL, GERANIUM MACULATUM OIL, ROSMARINUS OFFICINALIS (ROSEMARY) LEAF OIL, MENTHA PIPERITA (PEPPERMINT) OIL

PURPOSE

Purpose : Skin Protectant

WARNINGS

Warnings : Harmful if swallowed. Avoid contact with the eyes. Keep out of reach of children. In case of contact with eyes, rinse immediately with plenty of water and seek medical advice.

KEEP OUT OF REACH OF CHILDREN

INDICATIONS & USAGE

Indication and usage : After using the serum, apply the emulsion to the entire face evenly along the skin texture like massaging the entire face.

DOSAGE & ADMINISTRATION

Dosage and administration : Take a proper amount of the product, and spread it evenly over the entire face.